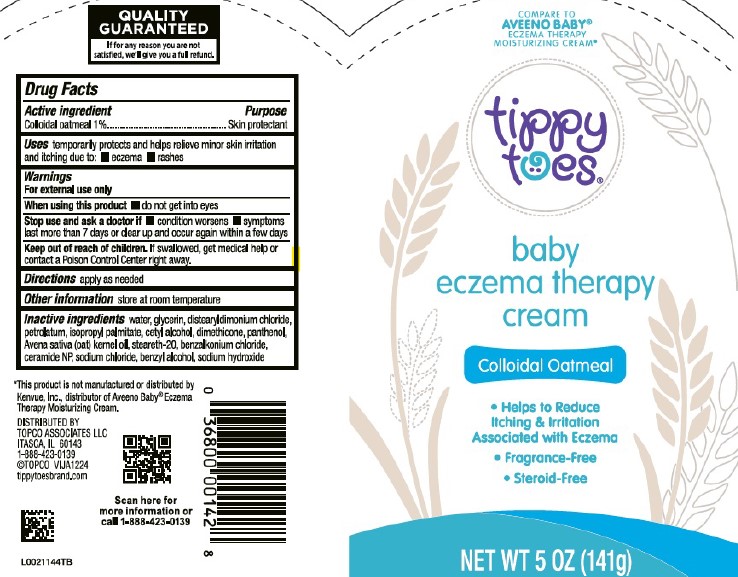 DRUG LABEL: Baby Eczema Therapy
NDC: 76162-601 | Form: CREAM
Manufacturer: Topco Associates LLC
Category: otc | Type: HUMAN OTC DRUG LABEL
Date: 20260213

ACTIVE INGREDIENTS: OATMEAL 1 mg/1 g
INACTIVE INGREDIENTS: WATER; GLYCERIN; DISTEARYLDIMONIUM CHLORIDE; PETROLATUM; ISOPROPYL PALMITATE; CETYL ALCOHOL; DIMETHICONE; PANTHENOL; OAT KERNEL OIL; STEARETH-20; BENZALKONIUM CHLORIDE; CERAMIDE NP; SODIUM CHLORIDE; BENZYL ALCOHOL; SODIUM HYDROXIDE

Tippy Toes 601.001/601AC
Baby Eczema Therapy Cream

Claims

QUALITY GUARANTEED

If for any reason you are not satisfied, we'll give you a full refund.

Active ingredient

Colloidal oatmeal 1%

Purpose

Skin protectant

Uses

temporarily protects and helps relieve minor skin irritation and itching due to:

- eczema
- rashes

Warnings

For external use only

When using this product

- do not get into eyes

Stop use and ask a doctor if

- condition worsens
- symptoms last more than 7 days or clear up and occur again within a few days

Keep out of reach of children

If swallowed, get medical help or contact a Poison Control Center right away.

Directions

apply as needed

Other information

store at room temperature

Inactive ingredients

water, glycerin, distearyldimonium chloride, petrolatum, isopropyl palmitate, cetyl alcohol, dimethicone, panthenol, Avena sativa (oat) kernel oil, steareth-20, benzalkonium chloride, ceramide NP, sodium chloride, benzyl alcohol, sodium hydroxide

Disclaimer

*This product is not manufactured or distributed by Kenvue, Inc., distributor of Aveeno Baby®Eczema Therapy Moisturizing Cream.

Adverse reaction

DISTRIBUTED BY

TOPCO ASSOCIATES LLC

ITASCA, IL 60143

1-888-423-0139

©TOPCO VIJA1224

tippytoesbrand.com

Scan here for more information or call 1-888-423-0139

Principal display panel

COMPARE TO AVEENO BABY® ECZEMA THERAPY MOISTURIZING CREAM*

tippy toes®

baby eczema therapy cream

Colloidal Oatmeal

- Helps to Reduce Itching & Irritation Associated with Eczema
- Fragrance-Free
- Steroid-Free

NET WT 5 OZ (141 g)